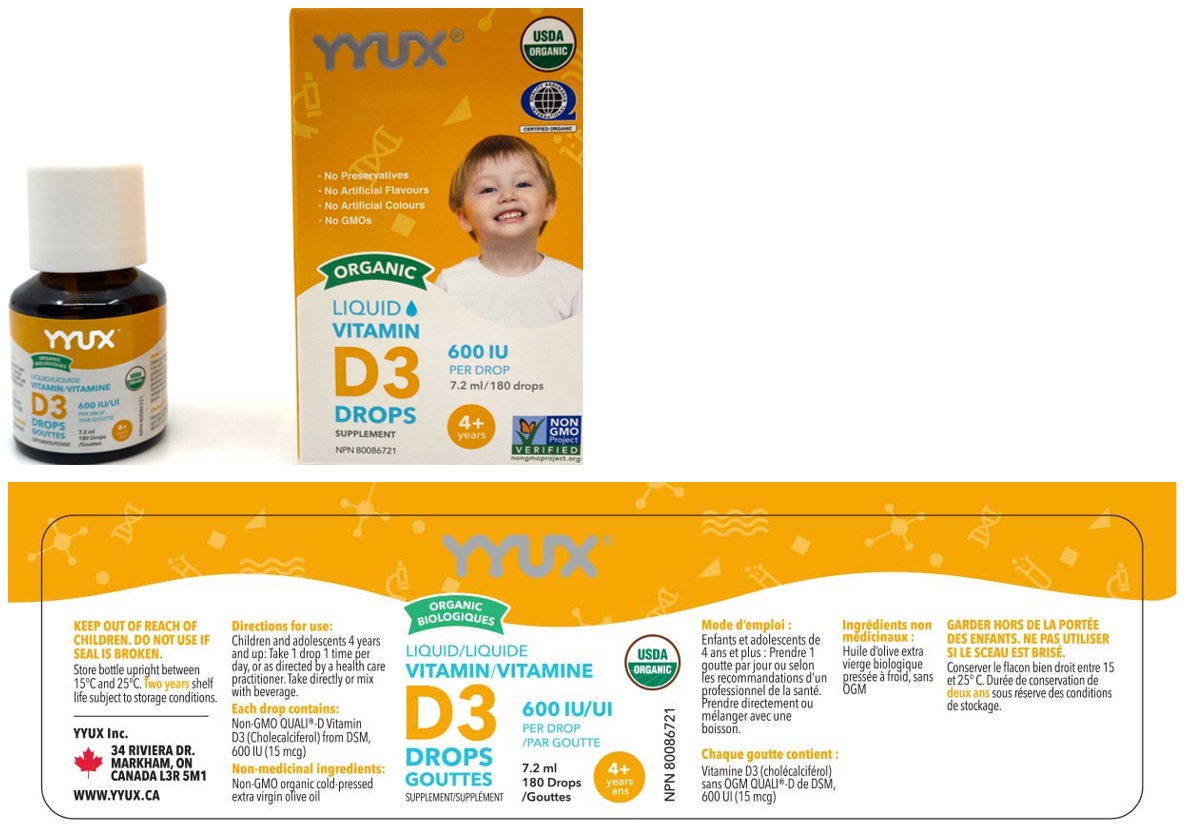 DRUG LABEL: YYUX Organic Liquid Vitamin D3 Drops For Kids 4 plus years 600 IU
NDC: 81303-600 | Form: SOLUTION/ DROPS
Manufacturer: Yyux Inc
Category: other | Type: DIETARY SUPPLEMENT
Date: 20201230

ACTIVE INGREDIENTS: CHOLECALCIFEROL 15 ug/0.04 mL
INACTIVE INGREDIENTS: OLIVE OIL

YYUX® ORGANIC LIQUID VITAMIN D3 DROPS SUPPLEMENT

Active Ingredient

Vitamin D3 (Cholecalciferol) 600IU (15ug per drop)

Supplement Facts; Serving Size: 1 drop; Serving Per Container: 180
Amount Per Serving | DV%
Calories 0
Total Fat 0 g | <1%
Cholesterol 0 mg | 0%
Vitamin D3 (Cholecalciferol) 15mcg (600IU) | 100%
Other ingredients: Olive Oil

Non-medicinal ingredients: Non-GMO organic cold-pressed extra virgin olive oil

Warnings:

KEEP OUT OF REACH OF CHILDREN. DO NOT USE IF SEAL IS BROKEN.

Storage:

Store bottle upright between 15°C and 25°C. Two years shelf life subject to storage conditions.

Directions for use:

Children and adolescents 4 years and up: Take 1 drop 1 time per day, or as directed by a health care practitioner. Take directly or mix with beverage.

A dropper supplied.

HEALTH CLAIM

A factor in the maintenance of good health. Helps in the development and maintenance of bones and teeth. Helps in the absorption and use of phosphorus and calcium.

Each drop contains: Non-GMO QUALI®-D Vitamin D3 (Cholecalciferol) from DSM, 600 IU (15 mcg)

USDA ORGANIC

QUALITY ASSURANCE INTERNATIONAL

CERTIFIED ORGANIC

NON GMO Project VERIFIED

nongmoproject.org

• No Preservatives

• No Artificial Flavours

• No Artificial Colours

• No GMOs
YYUX Inc.
34 RIVIERA DR.
MARKHAM, ON
CANADA L3R 5M1
WWW.YYUX.CA